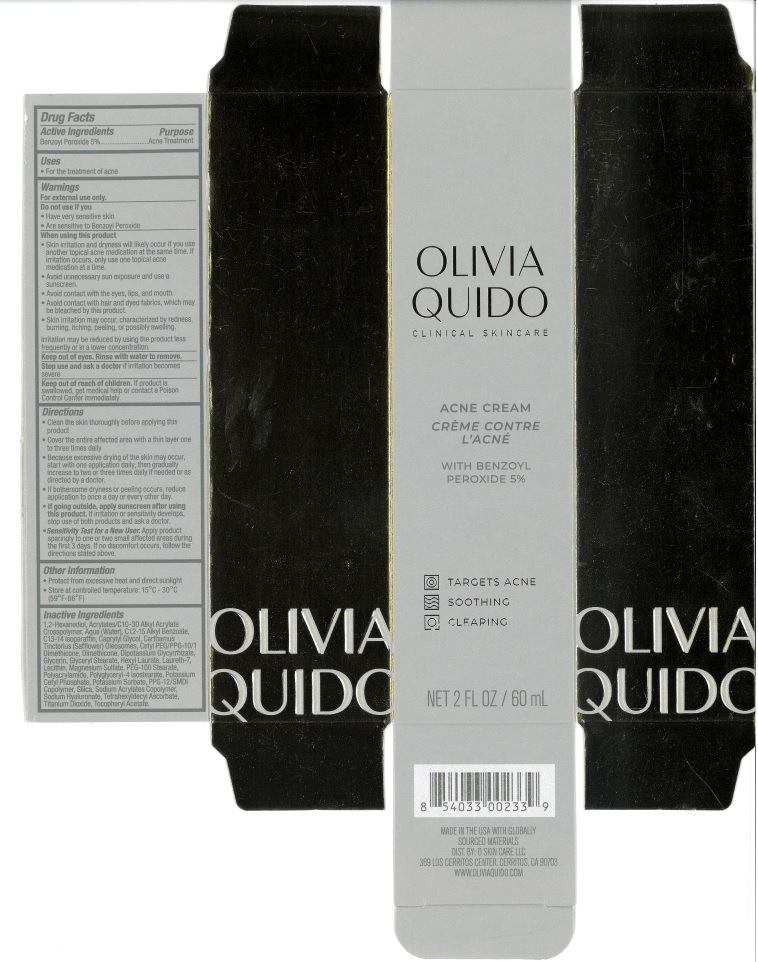 DRUG LABEL: Olivia Quido Acne Cream
NDC: 71421-902 | Form: CREAM
Manufacturer: O Skin Care LLC
Category: otc | Type: HUMAN OTC DRUG LABEL
Date: 20240822

ACTIVE INGREDIENTS: BENZOYL PEROXIDE 5 g/100 g
INACTIVE INGREDIENTS: CARTHAMUS TINCTORIUS (SAFFLOWER) OLEOSOMES; CAPRYLYL GLYCOL; CETYL PEG/PPG-10/1 DIMETHICONE (HLB 2); POLYACRYLAMIDE (10000 MW); WATER; PEG-100 STEARATE; MAGNESIUM SULFATE, UNSPECIFIED; POTASSIUM CETYL PHOSPHATE; 1,2-HEXANEDIOL; DIMETHICONE; GLYCERYL MONOSTEARATE; PPG-12/SMDI COPOLYMER; HEXYL LAURATE; HYALURONATE SODIUM; SILICON DIOXIDE; TITANIUM DIOXIDE; GLYCERIN; LAURETH-7; POTASSIUM SORBATE; TETRAHEXYLDECYL ASCORBATE; C13-14 ISOPARAFFIN; ALKYL (C12-15) BENZOATE; ALPHA-TOCOPHEROL ACETATE; POLYGLYCERYL-4 ISOSTEARATE; ACRYLATES/C10-30 ALKYL ACRYLATE CROSSPOLYMER (60000 MPA.S)

Olivia Quido Acne Cream

ACTIVE INGREDIENT

Benzoyl Peroxide 5%

PURPOSE

Acne Treatment

Uses

For the treatment of acne

WARNINGS

For external use only

DO NOT USE

• Have very sensitive skin
• Are sensitive to Benzoyl Peroxide

WHEN USING

• Skin irritation and dryness will likely occur if you use another topical acne medication at the same time. If irritation occurs, only use one topical acne medication at a time.
• Avoid urinecessary sun exposure and use a sunscreen.
• Avoid contact with the eyes, lips, and mouth.
• Avoid contact with hair and dyed fabrics, which may be bleached by this product.
• Skin irritation may occur, characterized by redness, burning, itching, peeling, or possibly swelling.
Irritation may be reduced by using the product less frequently or in a lower concentration.

Keep out of eyes. Rinse with water to remove.

Stop use and ask a doctor if irritation becomes severe

Keep out of reach of children. If product is swallowed, get medical help or contact a Poison Control Center immediately.

Directions
• Clean the skin thoroughly before applying this product
• Cover the entire affected area with a thin layer one to three times daily

INDICATIONS AND USAGE

• Because excessive drying of the skin may occur, start with one application daily, then gradually increase to two or three times daily if needed or as directed by a doctor.
• If bothersome dryness or peeling occurs, reduce application to once a day or every other day.
• If going outside, apply sunscreen after using this product. If irritation or sensitivity develops, stop use of both products and ask a doctor.
• Sensitivity Test for a New User. Apply product sparingly to one or two small affected areas during the first 3 days. If no discomfort occurs, follow the directions stated above.

Other Information
• Protect from excessive heat and direct sunlight
• Store at controlled temperature: 15°C -30°C (59°F-86°F)

Inactive Ingredients
1,2-Hexanediol, Acrylates/C10-30 Alkyl Acrylate Crosspolymer, Aqua (Water), C12-15 Alkyl Benzoate, C13-14 Isoparaffin, Caprylyl Glycol, Carthamus Tinctorius (Safflower) Oleosomes, Cetyl PEG/PPG-10/1 Dimethicone, Dimethicone, Dipotassium Glycyrrhizate, Glycerin, Glyceryl Stearate, Hexyl Laurate, Laureth-7, Lecithin, Magnesium Sulfate, PEG-100 Stearate, Polyacrylamide, Polyglyceryl-4 Isostearate, Potassium Cetyl Phosphate, Potassium Sorbate, PPG-12/SMDI Copolymer, Silica, Sodium Acrylates Copolymer, Sodium Hyaluronate, Tetrahexyldecyl Ascorbate, Titanium Dioxide, Tocopheryl Acetate.